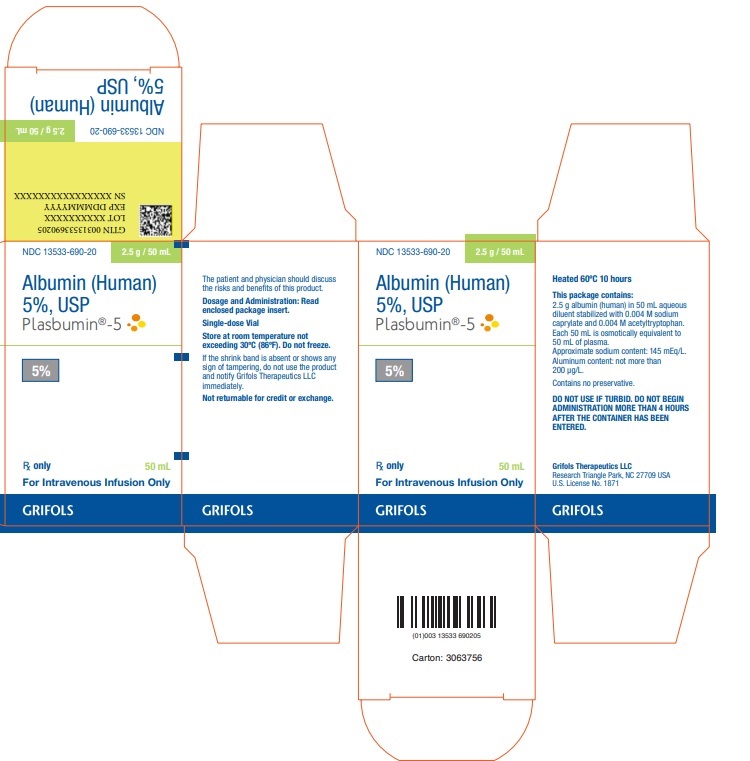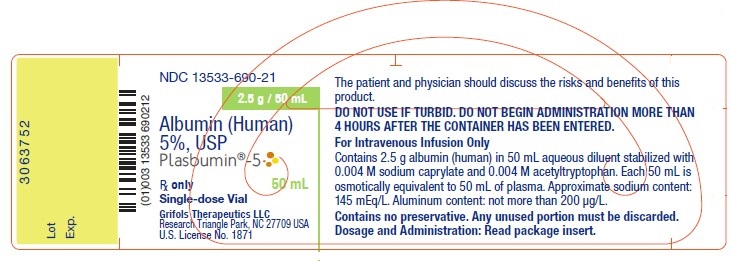 DRUG LABEL: Plasbumin 
NDC: 13533-690 | Form: SOLUTION
Manufacturer: GRIFOLS USA, LLC
Category: other | Type: PLASMA DERIVATIVE
Date: 20221118

ACTIVE INGREDIENTS: Albumin Human 2.5 g/50 mL
INACTIVE INGREDIENTS: Acetyltryptophan, Dl-; Sodium Caprylate; Water

Albumin (Human) 5%, USP
Plasbumin®-5

DESCRIPTION

Albumin (Human) 5%, USP (Plasbumin®-5) is made from large pools of human venous plasma by the Cohn cold ethanol fractionation process. Part of the fractionation may be performed by another licensed manufacturer. It is prepared in accordance with the applicable requirements established by the U.S. Food and Drug Administration.

Plasbumin-5 is a 5% sterile solution of albumin in an aqueous diluent. The preparation is stabilized with 0.004 M sodium caprylate and 0.004 M acetyltryptophan. The aluminum content of the product is not more than 200 µg/L. The approximate sodium content of the product is 145 mEq/L. Plasbumin-5 is clear, slightly viscous, almost colorless to yellow, amber or green. It contains no preservative. Plasbumin-5 must be administered intravenously.

Each vial of Plasbumin-5 is heat-treated at 60°C for 10 hours against the possibility of transmitting the hepatitis viruses.

Additionally, the manufacturing process was investigated for its capacity to decrease the infectivity of an experimental agent of transmissible spongiform encephalopathy (TSE), considered as a model for the variant Creutzfeldt-Jakob disease (vCJD) and Creutzfeldt-Jakob disease (CJD) agents.(8-11) The production steps from Pooled Plasma to Effluent IV-1 in the Plasbumin-5 manufacturing process have been shown to decrease TSE infectivity of that experimental model agent (a total of ≥7.0 logs). These studies provide reasonable assurance that low levels of vCJD/CJD agent infectivity, if present in the starting material, would be removed.

CLINICAL PHARMACOLOGY

Plasbumin-5 is oncotically equivalent volume for volume to normal human plasma.

When administered intravenously to an adequately hydrated subject, the oncotic (colloid osmotic) effect of Plasbumin-5 is to expand the circulating blood volume by an amount approximately equal to the volume infused. It is primarily used in the treatment of shock associated with hemorrhage, surgery, trauma, burns, bacteremia, renal failure, and cardiovascular collapse.(1)

Albumin is a transport protein and it may be useful in severe jaundice in hemolytic disease of the newborn.(1) This could also be of importance in acute liver failure where albumin might serve the dual role of supporting plasma oncotic pressure, as well as binding excessive plasma bilirubin.(1)

INDICATIONS AND USAGE

Emergency Treatment of Hypovolemic Shock

Plasbumin-5 is iso-oncotic with normal plasma and on intravenous infusion will expand the circulating blood volume by an amount approximately equal to the volume infused. In conditions associated mainly with a volume deficit, albumin is best administered as a 5% solution (Plasbumin-5); but where there is an oncotic deficit, Albumin (Human) 25%, USP (Plasbumin®-25) may be preferred. This is also an important consideration where the treatment of the shock state has been delayed. If Plasbumin-25 is used, appropriate additional crystalloid should be administered.(1)

Crystalloid solutions in volumes several times greater than that of Plasbumin-5 may be effective in treating shock in younger individuals who have no preexisting illness at the time of the incident. Older patients, especially those with preexisting debilitating conditions, or those in whom the shock is caused by a medical disorder, or where the state of shock has existed for some time before active therapy could be instituted, may not tolerate hypoalbuminemia as well.(1)

Removal of ascitic fluid from a patient with cirrhosis may cause changes in cardiovascular function and even result in hypovolemic shock. In such circumstances, the use of albumin infusion may be required to support the blood volume.(1)

Burn Therapy

An optimal therapeutic regimen with respect to the administration of colloids, crystalloids, and water following extensive burns has not been established. During the first 24 hours after sustaining thermal injury, large volumes of crystalloids are infused to restore the depleted extracellular fluid volume. Beyond 24 hours, albumin can be used to maintain plasma colloid osmotic pressure. Plasbumin-25 may be preferred for this purpose.(1)

Cardiopulmonary Bypass (1)

With the relatively small priming volume required with modern pumps, preoperative dilution of the blood using albumin and crystalloid has been shown to be safe and well-tolerated. Although the limit to which the hematocrit and plasma protein concentration can be safely lowered has not been defined, it is common practice to adjust the albumin and crystalloid pump prime to achieve a hematocrit of 20% and a plasma albumin concentration of 2.5 g per 100 mL in the patient.

Acute Liver Failure (1)

In the uncommon situation of rapid loss of liver function, with or without coma, administration of albumin may serve the double purpose of supporting the colloid osmotic pressure of the plasma as well as binding excess plasma bilirubin.

Sequestration of Protein Rich Fluids (2)

This occurs in such conditions as acute peritonitis, pancreatitis, mediastinitis, and extensive cellulitis. The magnitude of loss into the third space may require treatment of reduced volume or oncotic activity with an infusion of albumin.

Situations in Which Albumin Administration is Not Warranted (1)

In chronic nephrosis, infused albumin is promptly excreted by the kidneys with no relief of the chronic edema or effect on the underlying renal lesion. It is of occasional use in the rapid “priming” diuresis of nephrosis. Similarly, in hypoproteinemic states associated with chronic cirrhosis, malabsorption, protein losing enteropathies, pancreatic insufficiency, and undernutrition, the infusion of albumin as a source of protein nutrition is not justified.

CONTRAINDICATIONS

Certain patients, e.g., those with a history of congestive cardiac failure, renal insufficiency or stabilized chronic anemia, are at special risk of developing circulatory overload. A history of allergic reaction to albumin is a specific contraindication for usage.

WARNINGS

Plasbumin-5 is made from human plasma. Products made from human plasma may contain infectious agents, such as viruses, and, theoretically, the Creutzfeldt-Jakob Disease (CJD) agent that can cause disease. The theoretical risk for transmission of CJD is considered extremely remote. No cases of transmission of viral diseases or CJD have ever been identified for albumin. The risk that such products will transmit an infectious agent has been reduced by screening plasma donors for prior exposure to certain viruses, by testing for the presence of certain current virus infections, and by inactivating and/or removing certain viruses. Despite these measures, such products can still potentially transmit disease. There is also the possibility that unknown infectious agents may be present in such products. Individuals who receive infusions of blood or plasma products may develop signs and/or symptoms of some viral infections, particularly hepatitis C. ALL infections thought by a physician possibly to have been transmitted by this product should be reported by the physician or other healthcare provider to Grifols Therapeutics LLC [1-800-520-2807].

The physician should discuss the risks and benefits of this product with the patient, before prescribing or administering it to the patient.

Solutions which have been frozen should not be used. Do not use if turbid. Do not begin administration more than 4 hours after the container has been entered. Partially used vials must be discarded. Vials which are cracked or which have been previously entered or damaged should not be used, as this may have allowed the entry of microorganisms. Albumin (Human) 5%, USP (Plasbumin®-5) contains no preservative.

PRECAUTIONS

General

Patients should always be monitored carefully in order to guard against the possibility of circulatory overload. Plasbumin-5 is iso-oncotic with normal plasma and will not tend to aggravate tissue dehydration. Appropriate additional crystalloids should be administered, if required by the patient, to maintain normal fluid balance.

In hemorrhage, the administration of albumin should be supplemented by the transfusion of whole blood to treat the relative anemia associated with hemodilution.(3) When circulating blood volume has been reduced, hemodilution following the administration of albumin persists for many hours. In patients with a normal blood volume, hemodilution lasts for a much shorter period.(4-6) The rapid rise in blood pressure, which may follow the administration of a colloid with positive oncotic activity, necessitates careful observation to detect and treat severed blood vessels which may not have bled at the lower blood pressure.

Drug Interactions

Plasbumin-5 is compatible with whole blood and packed red cells, as well as the standard carbohydrate and electrolyte solutions intended for intravenous use. It should not be mixed with protein hydrolysates, amino acid solutions nor those containing alcohol.

Pregnancy

Animal reproduction studies have not been conducted with Plasbumin-5. It is also not known whether Plasbumin-5 can cause fetal harm when administered to a pregnant woman or can affect reproduction capacity. Plasbumin-5 should be given to a pregnant woman only if clearly needed.

Pediatric Use

Safety and effectiveness in the pediatric population have not been established.

ADVERSE REACTIONS

Adverse reactions to albumin are rare. Such reactions may be allergic in nature or be due to high plasma protein levels from excessive albumin administration. Allergic manifestations include urticaria, chills, fever, and changes in respiration, pulse and blood pressure.

DOSAGE AND ADMINISTRATION

Plasbumin-5 should always be administered by intravenous infusion. The choice between the use of Plasbumin-5 and Albumin (Human) 25%, USP (Plasbumin®-25) depends upon whether the patient requires primarily volume (Plasbumin-5) or primarily colloid osmotic activity (Plasbumin-25). Below a serum oncotic level of 20 mm Hg (equal to a total serum protein concentration of 5.2 g per 100 mL) there is evidence which suggests that the risk of complications increases.(1) When the oncotic pressure drops below this level, the patient should be treated with Plasbumin-25 together with diuretics. This is especially important in high risk patients who have undergone abdominal, cardiovascular, thoracic or urologic surgery or who have acute bacteremia.

The volume administered and the speed of administration should be adapted to the response of the individual patient.

A number of factors beyond our control could reduce the efficacy of this product or even result in an ill effect following its use. These include improper storage and handling of the product after it leaves our hands, diagnosis, dosage, method of administration, and biological differences in individual patients. Because of these factors, it is important that this product be stored properly and that the directions be followed carefully during use.

Hypovolemic Shock

The volume infused should be related to the estimated volume deficit and the speed of administration adapted to the response of the patient.

In neonates or infants, Plasbumin-5 may be given in large amounts.(7) The recommended dose is 10 to 20 mL/kg equivalent to 0.5 to 1.0 g albumin/kg body weight.

Burns

After a burn injury (usually beyond 24 hours) there is a close correlation between the amount of albumin infused and the resultant increase in plasma colloid osmotic pressure. The aim should be to maintain the plasma albumin concentration in the region of 2.5 ± 0.5 g per 100 mL with a plasma oncotic pressure of 20 mm Hg (equivalent to a total plasma protein concentration of 5.2 g per 100 mL).(1) This is best achieved by the intravenous administration of Plasbumin, usually as Plasbumin-25. The duration of therapy is decided by the loss of protein from burned areas and in the urine. In addition, oral or parenteral feeding with amino acids should be initiated, as the long-term administration of albumin should not be considered as a source of nutrition.

Other dosage recommendations are given under the specific indications referred to above.

Preparation for Administration

Remove seal to expose stopper. Always swab stopper top immediately with suitable antiseptic prior to entering vial.

Parenteral drug products should be inspected visually for particulate matter and discoloration prior to administration, whenever solution and container permit.

Only 16 gauge needles or dispensing pins should be used with 20 mL vial sizes and larger. Needles or dispensing pins should only be inserted within the stopper area delineated by the raised ring. The stopper should be penetrated perpendicular to the plane of the stopper within the ring.

HOW SUPPLIED

Plasbumin-5 is available in 50 mL, 250 mL, and 500 mL rubber-stoppered vials. Each single dose vial contains albumin in the following approximate amounts:

NDC Number | Size | Grams Albumin
13533-690-20 | 50 mL | 2.5
13533-690-25 | 250 mL | 12.5
13533-690-27 | 500 mL | 25

STORAGE

Store at room temperature not exceeding 30°C (86°F). Do not freeze. Do not use after expiration date.

Caution

Rx only

U.S. federal law prohibits dispensing without prescription.

REFERENCES

1. Tullis JL. Albumin. 1. Background and use. 2. Guidelines for clinical use. JAMA. 1977;237:355-60; 460-3.
2. Clowes GHA Jr, Vucinic M, Weidner MG. Circulatory and metabolic alterations associated with survival or death in peritonitis: clinical analysis of 25 cases. Ann Surg. 1966;163(6):866-85.
3. Heyl JT, Janeway CA. The use of human albumin in military medicine. I. The theoretical and experimental basis for its use. US Navy Med Bull. 1942;40:785-91.
4. Janeway CA, Gibson ST, Woodruff LM, Heyl JT Bailey OT, Newhouser LR. Chemical, clinical, and immunological studies on the products of human plasma fractionation. VII. Concentrated human serum albumin. J Clin Invest. 1944;23:465-90.
5. Woodruff LM, Gibson ST. The clinical evaluation of human albumin. US Navy Med Bull. 1942;40:791-6.
6. Janeway CA, Berenberg W, Hutchins G. Indications and uses of blood, blood derivatives and blood substitutes. Med Clin North Am. 1945;29:1069-94.
7. Bennett EJ. Fluid balance in the newborn. Anesthesiology. 1975;43:210-24.
8. Stenland CJ, Lee DC, Brown P, Petteway SR Jr, Rubenstein R. Partitioning of human and sheep forms of the pathogenic prion protein during the purification of therapeutic proteins from human plasma. Transfusion. 2002;42:1497-500.
9. Lee DC, Stenland CJ, Miller JL, Cai K, Ford EK, Gilligan KJ, et al. A direct relationship between the partitioning of the pathogenic prion protein and transmissible spongiform encephalopathy infectivity during the purification of plasma proteins. Transfusion. 2001;41:449-55.
10. Lee DC, Stenland CJ, Hartwell RC, Ford EK, Cai K, Miller JL, et al. Monitoring plasma processing steps with a sensitive Western blot assay for the detection of the prion protein. J Virol Methods. 2000;84:77-89.
11. Cai K, Miller JL, Stenland CJ, Gilligan KJ, Hartwell RC, Terry JC, et al. Solvent-dependent precipitation of prion protein. Biochim Biophys Acta. 2002;1597:28-35.

GRIFOLS
Grifols Therapeutics LLC
Research Triangle Park, NC 27709 USA
U.S. License No. 1871

3060200
(Rev. 8/2020)

PACKAGE LABEL

NDC 13533-690-20 2.5 g / 50 mL
Albumin (Human)
5%, USP
Plasbumin®-5
5%
Rx only 50 mL
For Intravenous Infusion Only
GRIFOLS
Heated 60°C 10 hours
This package contains:
2.5 g albumin (human) in 50 mL aqueous
diluent stabilized with 0.004 M sodium
caprylate and 0.004 M acetyltryptophan.
Each 50 mL is osmotically equivalent to
50 mL of plasma.
Approximate sodium content: 145 mEq/L.
Aluminum content: not more than
200 μg/L.
Contains no preservative.
DO NOT USE IF TURBID. DO NOT BEGIN
ADMINISTRATION MORE THAN 4 HOURS
AFTER THE CONTAINER HAS BEEN
ENTERED.
Grifols Therapeutics LLC
Research Triangle Park, NC 27709 USA
U.S. License No. 1871
GRIFOLS
NDC 13533-690-20 2.5 g / 50 mL
Albumin (Human)
5%, USP
Plasbumin®-5
5%
Rx only 50 mL
For Intravenous Infusion Only
GRIFOLS
The patient and physician should discuss
the risks and benefits of this product.
Dosage and Administration: Read
enclosed package insert.
Single-dose Vial
Store at room temperature not
exceeding 30°C (86°F). Do not freeze.
If the shrink band is absent or shows any
sign of tampering, do not use the product
and notify Grifols Therapeutics LLC
immediately.
Not returnable for credit or exchange.
GRIFOLS
GTIN 00313533690205
LOT XXXXXXXXXX
EXP DDMMMYYYY
SN XXXXXXXXXXXXXXXX
NDC 13533-690-20 2.5 g / 50 mL
Albumin (Human)
5%, USP
Carton: 3063756

NDC 13533-690-21 2.5 g / 50 mL
Albumin (Human)
5%, USP
Plasbumin®-5
Rx only 50 mL
Single-dose Vial
Grifols Therapeutics LLC
Research Triangle Park, NC 27709 USA
U.S. License No. 1871
The patient and physician should discuss the risks and benefits of this
product.
DO NOT USE IF TURBID. DO NOT BEGIN ADMINISTRATION MORE THAN
4 HOURS AFTER THE CONTAINER HAS BEEN ENTERED.
For Intravenous Infusion Only
Contains 2.5 g albumin (human) in 50 mL aqueous diluent stabilized with
0.004 M sodium caprylate and 0.004 M acetyltryptophan. Each 50 mL is
osmotically equivalent to 50 mL of plasma. Approximate sodium content:
145 mEq/L. Aluminum content: not more than 200 μg/L.
Contains no preservative. Any unused portion must be discarded.
Dosage and Administration: Read package insert.
3063752
Lot
Exp.